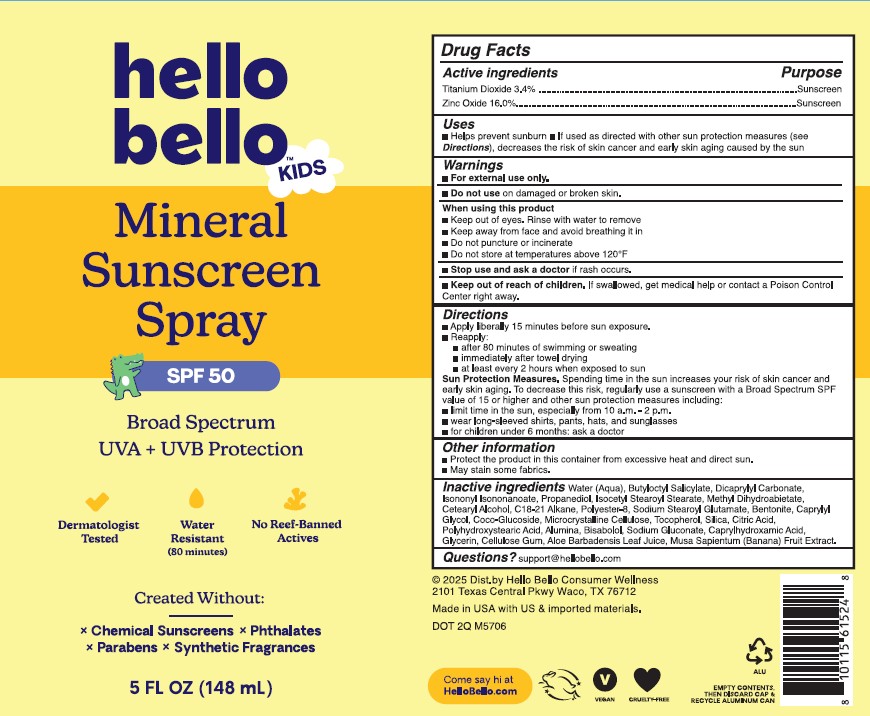 DRUG LABEL: Kids Mineral Sunscreen SPF50
NDC: 73418-105 | Form: SPRAY
Manufacturer: Hello Bello
Category: otc | Type: HUMAN OTC DRUG LABEL
Date: 20251002

ACTIVE INGREDIENTS: ZINC OXIDE 160 mg/1 g; TITANIUM DIOXIDE 34 mg/1 g
INACTIVE INGREDIENTS: WATER; ISONONYL ISONONANOATE; POLYESTER-8 (1400 MW, CYANODIPHENYLPROPENOYL CAPPED); ISOCETYL STEAROYL STEARATE; C18-C21 ALKANE; DICAPRYLYL CARBONATE; METHYL DIHYDROABIETATE; SODIUM STEAROYL GLUTAMATE; SILICON DIOXIDE; ALUMINUM OXIDE; CITRIC ACID MONOHYDRATE; MICROCRYSTALLINE CELLULOSE; CARBOXYMETHYLCELLULOSE SODIUM; LEVOMENOL; POLYHYDROXYSTEARIC ACID STEARATE; SODIUM GLUCONATE; TOCOPHEROL; GLYCERIN; CAPRYLHYDROXAMIC ACID; ALOE VERA LEAF; CETOSTEARYL ALCOHOL; CAPRYLYL GLYCOL; BUTYLOCTYL SALICYLATE; PROPANEDIOL; COCO GLUCOSIDE; BANANA

Mineral Sunscreen Spray SPF50

Active Ingredients

Titanium Dioxide 3.4%

Zinc Oxide 16%

Purpose

Sunscreen

Uses

- Helps prevent sunburn
- If used as directed with other sun protection measures (see Directions), decreases the risk of skin cancer and early skin aging caused by the sun

Warnings

For external use only

Flammable: Do not use near heat, flame, or while smoking

Do not use on

broken or damaged skin

When using this product

Keep away from face and avoid breathing it. Keep out of eyes. Rinse with water to remove. Do not puncture or incinerate. Contents under pressure. Do not store at temperatures above 120F.

Stop use and ask a doctor

if rash occurs

Keep out of reach of children.

If swallowed, get medical help or contact a Poison Control Center right away

Directions

- Shake well before use
- Apply liberally and spread evenly by hand 15 minutes before sun exposure
- Hold 4 to 6 inches away from body when spraying
- For children under 6 months of age, ask a doctor
- Do not spray directly on face
- Spray on hand and apply to face. Use in well-ventilated areas. Do not apply in wind conditions.
- Reapply: • after 80 minutes of swimming or sweating • immediately after towel use • at least every 2 hours
- Sun Protection Measures: Spending time in the sun can increase your risk of skin cancer and early skin aging. To decrease this risk, regularly use sunscreen with a Broad Spectrum SPF value of 15 or higher and other sun protection measures including: • Limit time in the sun, especially from 10a.m. - 2p.m. • Wear long-sleeved shirts, pants, hats and sunglasses

Other Information

- Protect this product from excessive heat and direct sun
- May stain some fabrics

Inactive Ingredients

Water (Aqua), Butyloctyl Salicylate, Isononyl Isnonanoate, Dicaprylyl Carbonate, Methyl Dihydroabietate, Propanediol, Isocetyl Stearoyl Stearate, Cetearyl Alcohol, Sodium Stearoyl Glutamate, Polyester-8, C18-21 Alkane, Silica, Alumina, Tocopherol, Bisabolol, Polyhydroxystearic Acid, Coco-Glucoside, Glycerin, Caprylyl Glycol, Caprylhydroxamic Acid, Musa Sapientum (Banana) Fruit Extract, Sodium Gluconate, Citric Acid, Aloe Barbadensis Leaf Juice, Bentonite, Microcrystalline Cellulose, Cellulose Gum